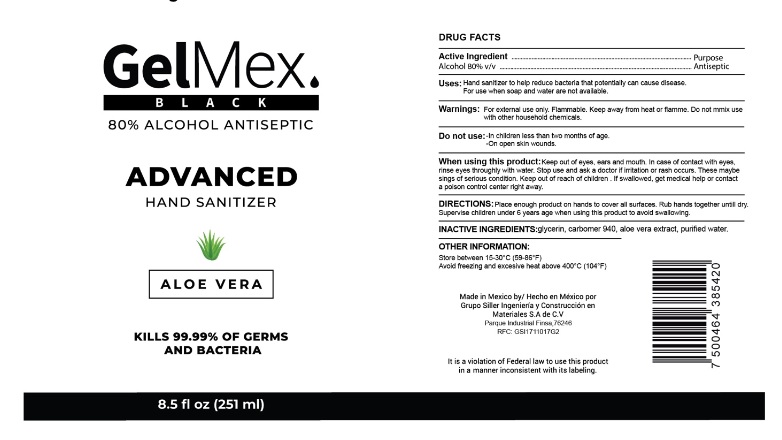 DRUG LABEL: GelMex Black
NDC: 80308-001 | Form: GEL
Manufacturer: Grupo Siller Ingeniería Construcción y Materiales, S.A. de C.V
Category: otc | Type: HUMAN OTC DRUG LABEL
Date: 20200904

ACTIVE INGREDIENTS: ALCOHOL 80 mL/100 mL
INACTIVE INGREDIENTS: WATER; GLYCERIN; CARBOMER 940; ALOE VERA LEAF

GelMex Black

Active Ingredient

Alcohol 80%v/v

Purposes

Antiseptic

Uses

- Hand sanitizer to help reduce bacteria that potentially can cause disease.
- For use when soap and water are not available.

Warnings

For external use only. Flammable. Keep away from heat or flamme.

Do not mix use with other household chemicals.

Do not use

- In children less than two months of age.
- On open skin wounds.

When using this product:

- Keep out of eyes, ears and mouth. In case of contact with eyes, rinse eyes throughly with water.

Stop use and ask a doctor if irritation or rash occurs. These maybe sings of serious condition.

Keep out of reach of children

If swallowed, get medical help or contact a poison control center right away.

DOSAGE AND ADMINISTRATION

- Place enough product on hands to cover all surfaces. Rub hands together untill dry.
- Supervise children under 6 years age when using this product to avoid swallowing.

undefined

- Store between 15-30°C (59-86°F)
- Avoid freezing and excesive heat above 400°C (104°F)

Inactive ingredients

Glycerin, carbomer 940, aloe vera extract, purified water.